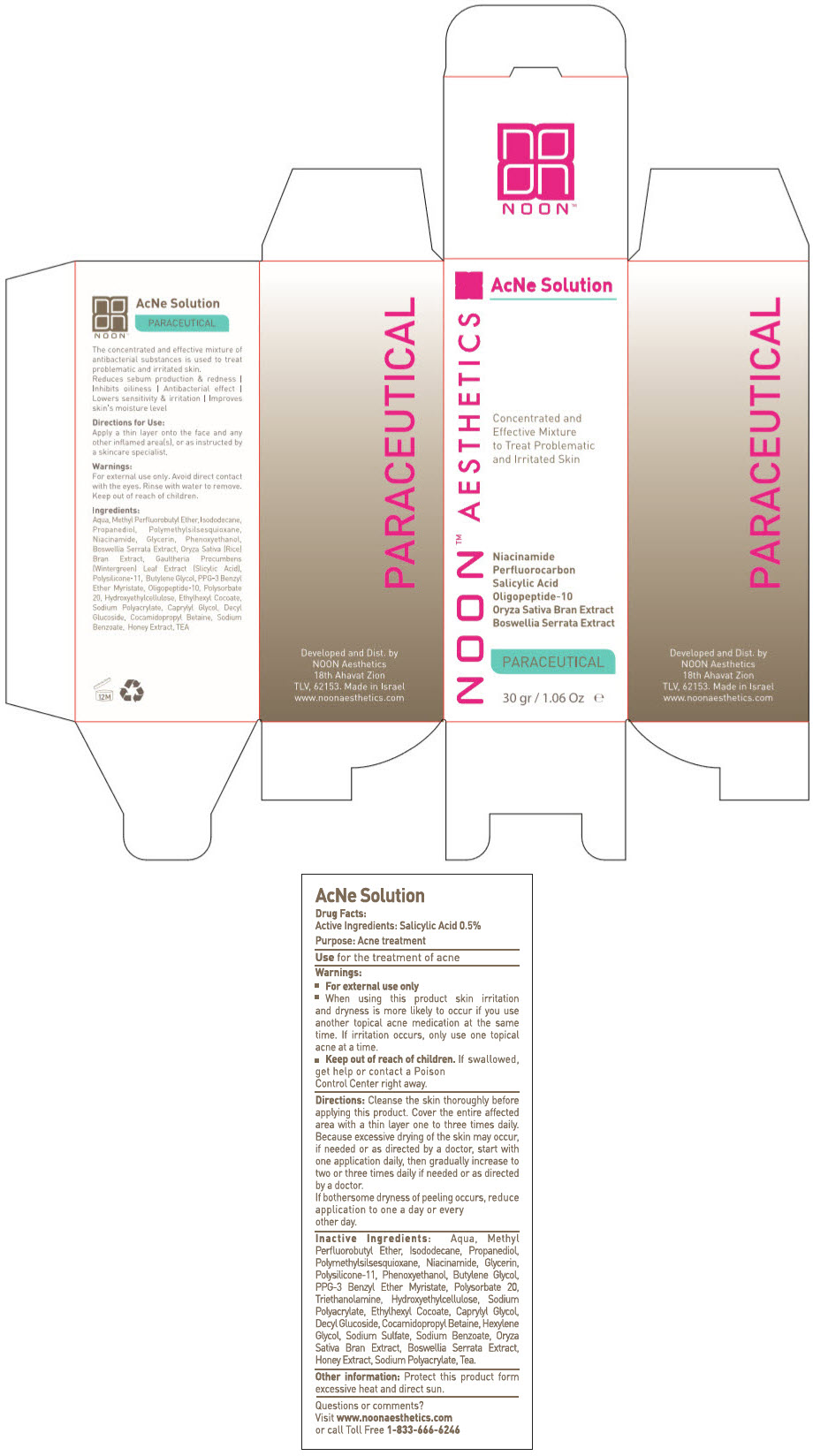 DRUG LABEL: AcNe solution
NDC: 78863-1220 | Form: CREAM
Manufacturer: Noon Aesthetics M.R. Ltd
Category: otc | Type: HUMAN OTC DRUG LABEL
Date: 20250113

ACTIVE INGREDIENTS: Salicylic Acid 0.15 g/30 g
INACTIVE INGREDIENTS: Methyl Perfluorobutyl Ether; Isododecane; Water; DIMETHICONE/VINYL DIMETHICONE CROSSPOLYMER (SOFT PARTICLE); Butylene Glycol; Decyl Glucoside; POLYMETHYLSILSESQUIOXANE (4.5 MICRONS); HYDROXYETHYL CELLULOSE, UNSPECIFIED; Niacinamide; Polysorbate 20; Cocamidopropyl Betaine; Glycerin; SODIUM POLYACRYLATE (8000 MW); ETHYLHEXYL COCOATE; PPG-3 Benzyl Ether Myristate

AcNe Solution

Drug Facts

Active Ingredients

Salicylic Acid 0.5%

Purpose

Acne treatment

INDICATIONS AND USAGE

Use for the treatment of acne

Warnings

- For external use only
- When using this product skin irritation and dryness is more likely to occur if you use another topical acne medication at the same time. If irritation occurs, only use one topical acne at a time.

- Keep out of reach of children. If swallowed, get help or contact a Poison Control Center right away.

Directions

Cleanse the skin thoroughly before applying this product. Cover the entire affected area with a thin layer one to three times daily. Because excessive drying of the skin may occur, if needed or as directed by a doctor. Start with one application daily, then gradually increase to two or three times daily if needed or as directed by a doctor.

If bothersome dryness of peeling occurs, reduce application to one a day or every other day.

Inactive Ingredients

Aqua, Methyl Perfluorobutyl Ether, Isododecane, Propanediol, Polymethylsilsesquioxane, Niacinamide, Glycerin, Polysilicone-11, Phenoxyethanol, Butylene Glycol, PPG-3 Benzyl Ether Myristate, Polysorbate 20, Triethanolamine, Hydroxyethylcellulose, Sodium Polyacrylate, Ethylhexyl Cocoate, Caprylyl Glycol, Decyl Glucoside, Cocamidopropyl Betaine, Hexylene Glycol, Sodium Sulfate, Sodium Benzoate, Oryza Sativa Bran Extract, Boswellia Serrata Extract, Honey Extract, Sodium Polyacrylate, Tea.

Other information

Protect this product form excessive heat and direct sun.

Questions or comments? Visit www.noonaesthetics.com or call Toll Free 1-833-666-6246

Dist. by
NOON Aesthetics
18th Ahavat Zion
TLV, 62153.

PRINCIPAL DISPLAY PANEL - 30 g Bottle Carton

NOON™ AESTHETICS

AcNe Solution

Concentrated and
Effective Mixture
to Treat Problematic
and Irritated Skin

Niacinamide
Perfluorocarbon
Salicyclic Acid
Oligopeptide-10
Oryza Sativa Bran Extract
Boswellia Serrata Extract

PARACEUTICAL

30 gr / 1.06 Oz e